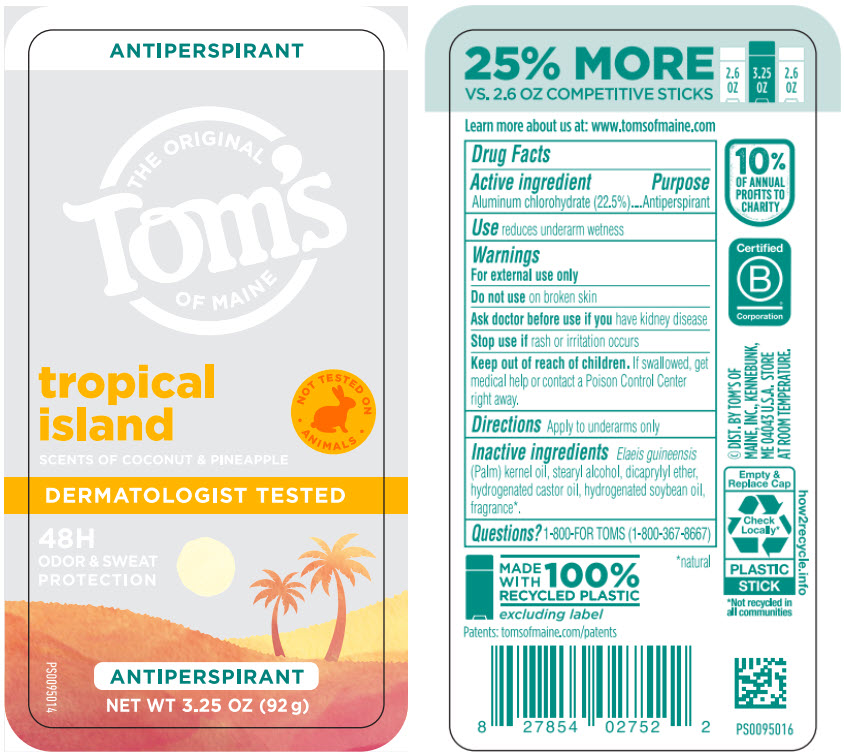 DRUG LABEL: Toms of Maine
NDC: 51009-861 | Form: STICK
Manufacturer: Tom's of Maine
Category: otc | Type: HUMAN OTC DRUG LABEL
Date: 20260127

ACTIVE INGREDIENTS: ALUMINUM CHLOROHYDRATE 225 mg/1 g
INACTIVE INGREDIENTS: PALM KERNEL OIL; STEARYL ALCOHOL; DICAPRYLYL ETHER; HYDROGENATED CASTOR OIL; HYDROGENATED SOYBEAN OIL

Tom's of Maine
Tropical Island

Drug Facts

Active ingredient

Aluminum chlorohydrate (22.5%)

Purpose

Antiperspirant

Use

reduces underarm wetness

Warnings

For external use only

Do not use on broken skin

Ask doctor before use if you have kidney disease

Stop use if rash or irritation occurs

Keep out of reach of children. If swallowed, get medical help or contact a Poison Control Center right away.

Directions

Apply to underarms only

Inactive ingredients

Elaeis guineensis (Palm) kernel oil, stearyl alcohol, dicaprylyl ether, hydrogenated castor oil, hydrogenated soybean oil, fragrance [natural] .

Questions?

1-800-FOR TOMS (1-800-367-8667)

DIST. BY TOM'S OF
MAINE, INC., KENNEBUNK,
ME 04043 U.S.A.

PRINCIPAL DISPLAY PANEL - 92 g Container Label

ANTIPERSPIRANT

THE ORIGINAL
Tom's
OF MAINE

tropical
island

NOT TESTED ON
∙ ANIMALS ∙

SCENTS OF COCONUT & PINEAPPLE

DERMATOLOGIST TESTED

48H
ODOR & SWEAT
PROTECTION

PS0095014

ANTIPERSPIRANT

NET WT 3.25 OZ (92 g)